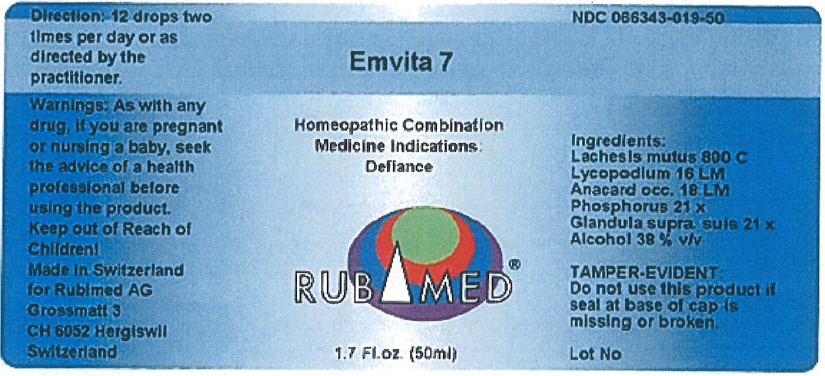 DRUG LABEL: Emvita 7
NDC: 66343-019 | Form: LIQUID
Manufacturer: RUBIMED AG
Category: otc | Type: HUMAN OTC DRUG LABEL
Date: 20150709

ACTIVE INGREDIENTS: Lachesis Muta Venom 800 [hp_C]/1 mL; Lycopodium Clavatum Spore 16 [hp_M]/1 mL; Anacardium Occidentale Fruit 18 [hp_M]/1 mL; Phosphorus 21 [hp_X]/1 mL; Sus Scrofa Adrenal Gland 21 [hp_X]/1 mL
INACTIVE INGREDIENTS: Alcohol 0.38 mL/1 mL

Emvita 7

PURPOSE

Homeopathic Combination Medicine Indications: Defiance

Ingredients

INACTIVE INGREDIENT

Lachesis mutus 800 C
Lycopodium 16 LM
Anacard occ. 18 LM
Phosphorus 2l x
Glandula supra. suis 21 x
Alcohol 38 % v/v

TAMPER-EVIDENT

Do not use this product if seal at base of cap is missing or broken.

Direction

12 drops two times per day or as directed by the practitioner.

Warnings

PREGNANCY OR BREAST FEEDING

As with any drug, if you are pregnant or nursing a baby, seek the advice of a health professional before using the product.

Keep out of Reach of Children!

PRINCIPAL DISPLAY PANEL - 50 ml Bottle Label

Emvita 7

Homeopathic Combination
Medicine Indications:
Defiance

RUBIMED®

1.7 Fl.oz. (50ml)